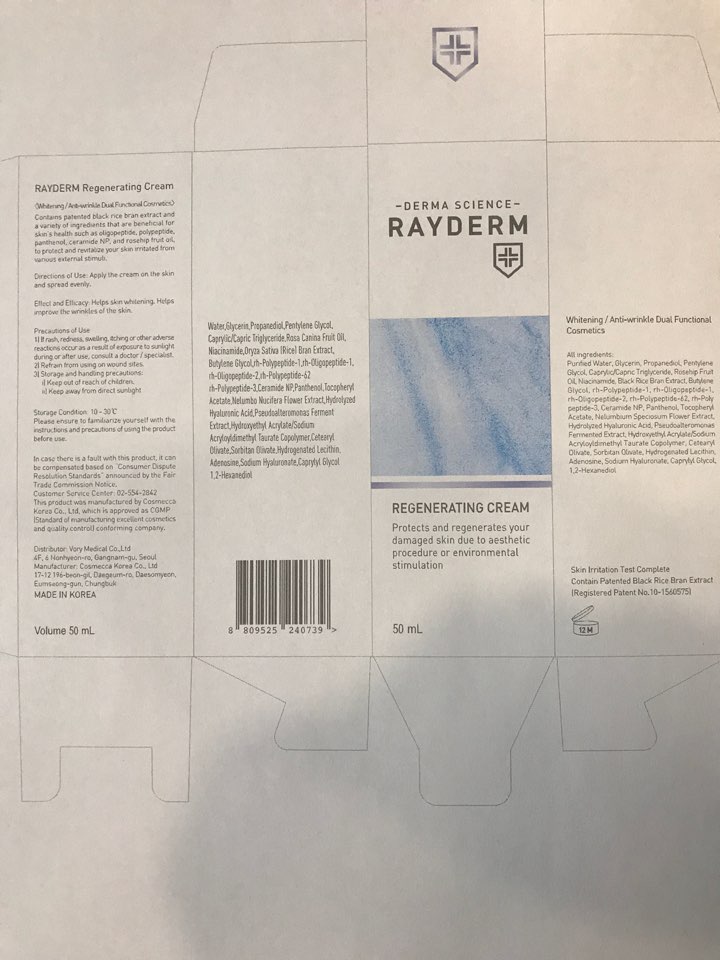 DRUG LABEL: Rayderm Re-generating Cream
NDC: 72543-002 | Form: CREAM
Manufacturer: VORY MEDICAL. Inc
Category: otc | Type: HUMAN OTC DRUG LABEL
Date: 20181011

ACTIVE INGREDIENTS: glycerin 12.5 g/50 mL
INACTIVE INGREDIENTS: water; PROPANEDIOL; PENTYLENE GLYCOL; NIACINAMIDE; ROSA CANINA FRUIT OIL; HYDROXYETHYL ACRYLATE/SODIUM ACRYLOYLDIMETHYL TAURATE COPOLYMER (45000 MPA.S AT 1%); PANTHENOL; CETEARYL OLIVATE; SORBITAN OLIVATE; CERAMIDE NP; BUTYLENE GLYCOL; NELUMBO NUCIFERA FLOWER; ADENOSINE; 1,2-HEXANEDIOL; CAPRYLYL GLYCOL

ACTIVE INGREDIENT

Glycerin (25.003%) - Skin Protectact

INACTIVE INGREDIENT

Purified Water, Propanediol, Pentylene Glycol, Caprylic/Capric Triglyceride, Rosehip Fruit Oil, Niacinamide, Black Rice Bran Extract, Butylene Glycol, rh-Polypeptide-1, rh-Oligopeptide-1, rh-Oligopeptide-2, rh-Polypeptide-62, rh-Polypeptide-3, Ceramide NP, Panthenol, Tocopheryl Acetate, Nelumbium Speciosum Flower Extract, Hydrolyzed Hyaluronic Acid, Pseudoalteromonas Fermented Extract, Hydroxyethyl Acrylate/Sodium Acryloyldimethyl Taurate Copolymer, Cetearyl Olivate, Sorbitan Olivate, Hydrogenated Lecithin, Adenosine, Sodium Hyaluronate, Caprylyl Glycol, 1,2-Hexanediol

PURPOSE

Skin Protectact

WARNINGS

Precautions of Use
1) If rash, redness, swelling, itching or other adverse reactions occur as a result of exposure to sunlight during or after use, consult a doctor / specialist.
2) Refrain from using on wound sites.
3) Storage and handling precautions:
i) Keep out of reach of children.
ii) Keep away from direct sunlight

INDICATIONS & USAGE

Apply the cream on the skin and spread evenly.

DOSAGE & ADMINISTRATION

Apply the cream on the skin and spread evenly.